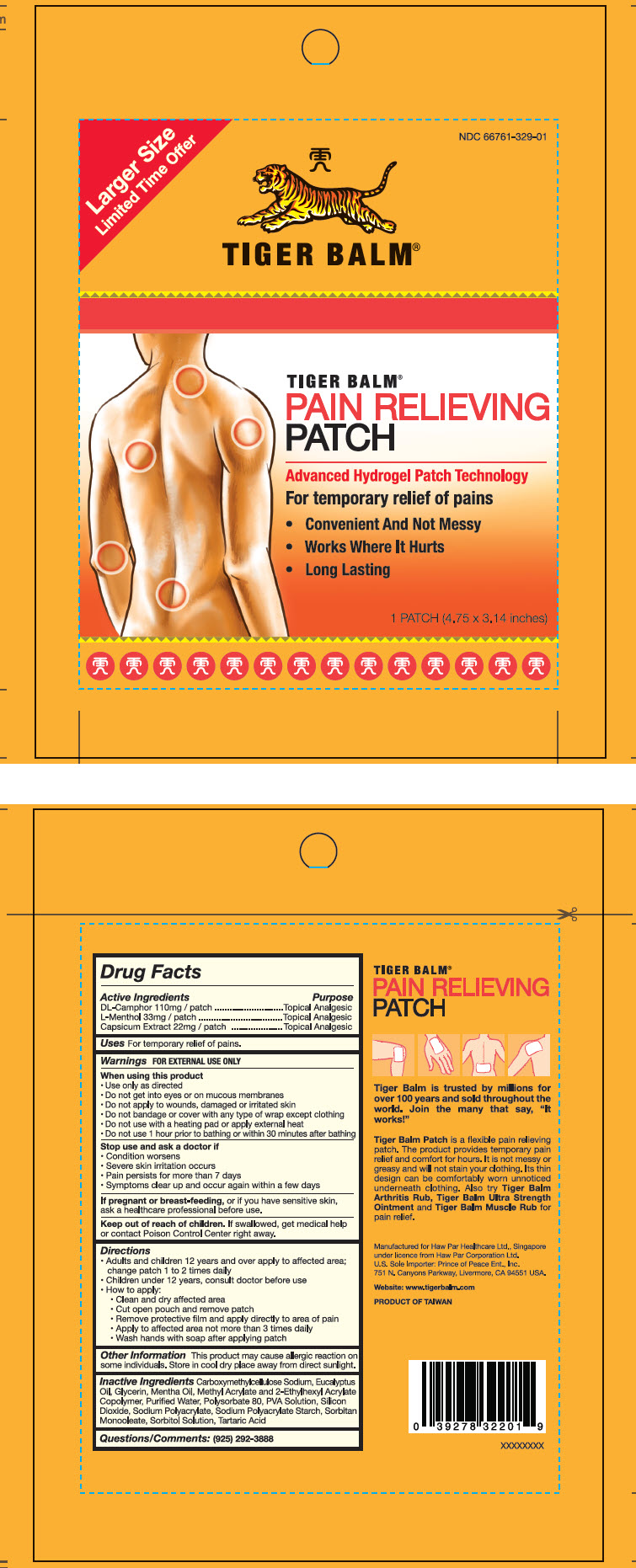 DRUG LABEL: TIGER BALM 
NDC: 66761-329 | Form: PATCH
Manufacturer: Haw Par Healthcare Ltd.
Category: otc | Type: HUMAN OTC DRUG LABEL
Date: 20250715

ACTIVE INGREDIENTS: Camphor (Synthetic) 110 mg/1 1; Levomenthol 33 mg/1 1; Capsicum 22 mg/1 1
INACTIVE INGREDIENTS: Carboxymethylcellulose Sodium, Unspecified; Eucalyptus Oil; Glycerin; Water; Polysorbate 80; Silicon Dioxide; Sorbitan Monooleate; Sorbitol; Tartaric Acid

TIGER BALM®
PAIN RELIEVING PATCH

Drug Facts

ACTIVE INGREDIENT

Active Ingredients | Purpose
DL-Camphor 110mg / patch | Topical Analgesic
L-Menthol 33mg / patch | Topical Analgesic
Capsicum Extract 22mg / patch | Topical Analgesic

Uses

For temporary relief of pains.

Warnings

FOR EXTERNAL USE ONLY

When using this product

- Use only as directed
- Do not get into eyes or on mucous membranes
- Do not apply to wounds, damaged or irritated skin
- Do not bandage or cover with any type of wrap except clothing
- Do not use with a heating pad or apply external heat
- Do not use 1 hour prior to bathing or within 30 minutes after bathing

Stop use and ask a doctor if

- Condition worsens
- Severe skin irritation occurs
- Pain persists for more than 7 days
- Symptoms clear up and occur again within a few days

PREGNANCY OR BREAST FEEDING

If pregnant or breast-feeding, or if you have sensitive skin, ask a healthcare professional before use.

Keep out of reach of children. If swallowed, get medical help or contact Poison Control Center right away.

Directions

- Adults and children 12 years and over apply to affected area; change patch 1 to 2 times daily
- Children under 12 years, consult doctor before use
- How to apply:
  - Clean and dry affected area
  - Cut open pouch and remove patch
  - Remove protective film and apply directly to area of pain
  - Apply to affected area not more than 3 times daily
  - Wash hands with soap after applying patch

Other Information

This product may cause allergic reaction on some individuals. Store in cool dry place away from direct sunlight.

Inactive Ingredients

Carboxymethylcellulose Sodium, Eucalyptus Oil, Glycerin, Mentha Oil, Methyl Acrylate and 2-Ethylhexyl Acrylate Copolymer, Purified Water, Polysorbate 80, PVA Solution, Silicon Dioxide, Sodium Polyacrylate, Sodium Polyacrylate Starch, Sorbitan Monooleate, Sorbitol Solution, Tartaric Acid

Questions/Comments

(925) 292-3888

PRINCIPAL DISPLAY PANEL - 1 Patch Box

Larger Size
Limited Time Offer

NDC 66761-329-01

TIGER BALM®

TIGER BALM®
PAIN RELIEVING
PATCH

Advanced Hydrogel Patch Technology

For temporary relief of pains

- Convenient And Not Messy
- Works Where It Hurts
- Long Lasting

1 PATCH (4.75 x 3.14 inches)